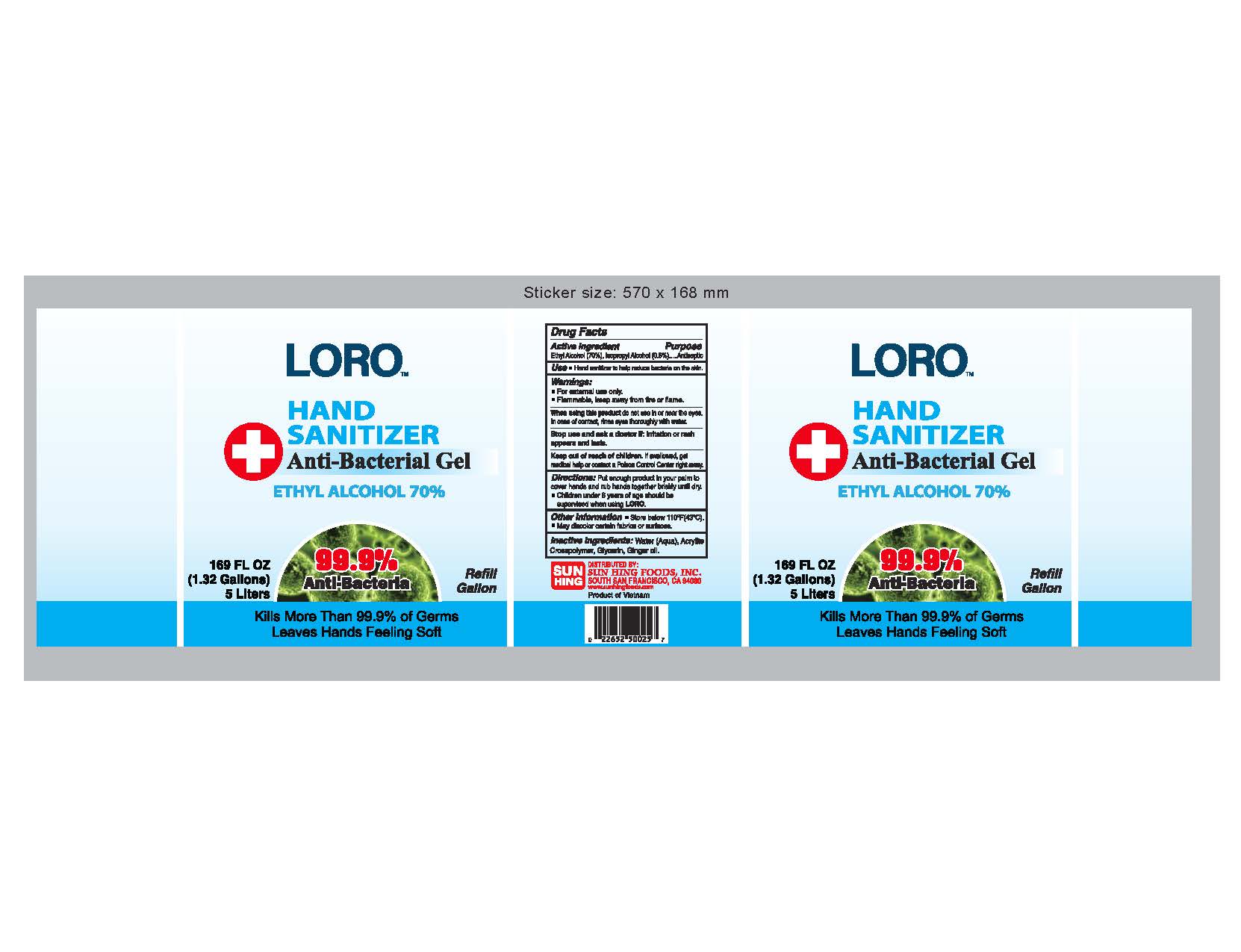 DRUG LABEL: Hand Sanitizer
NDC: 78185-004 | Form: GEL
Manufacturer: Sun Hing Foods Inc
Category: otc | Type: HUMAN OTC DRUG LABEL
Date: 20200618

ACTIVE INGREDIENTS: ALCOHOL 80 mL/100 mL
INACTIVE INGREDIENTS: GLYCERIN 1.45 mL/100 mL; HYDROGEN PEROXIDE 0.125 mL/100 mL; WATER

LORO
HAND SANITIZER
Anti-Bacterial Gel
ETHYL ALCOHOL 70%

This is a hand sanitizer manufactured according to the Temporary Policy for Preparation of Certain Alcohol-Based Hand Sanitizer Products During the Public Health Emergency (CoViD-19); Guidance for Industry.

The hand sanitizer is manufactured using only the following United States Pharmacopoeia (USP) grade ingredients in the preparation of the product (percentage in final product formulation) consistent with World Health Organization (WHO) recommendations:

1. Alcohol (ethanol) (USP or Food Chemical Codex (FCC) grade) (80%, volume/volume (v/v)) in an aqueous solution denatured according to Alcohol and Tobacco Tax and Trade Bureau regulations in 27 CFR part 20.
2. Glycerol (1.45% v/v).
3. Hydrogen peroxide (0.125% v/v).
4. Sterile distilled water or boiled cold water.

The firm does not add other active or inactive ingredients. Different or additional ingredients may impact the quality and potency of the product.

Active Ingredient(s)

Ethyl Alcohol 70%, Isopropyl Alcohol 0.5%. Purpose: Antiseptic

Purpose

Antiseptic, Hand Sanitizer

Use

Hand Sanitizer to help reduce bacteria on the skin.

Warnings

For external use only. Flammable. Keep away from fire or flame

Do not use

- Children under 6 years of age should be supervised when using LORO

When using this product

do not use in or near eyes. In case of contact with eyes, rinse eyes thoroughly with water.
Stop use and ask a doctor if irritation or rash appears and lasts.
Keep out of reach of children. If swallowed, get medical help or contact a Poison Control Center right away.

Stop use and ask a doctor if:

irritation or rash appears and lasts.

Keep out of reach of children. If swallowed, get medical help or contact a Poison Control Center right away.

Directions

- Place enough product on hands to cover all surfaces. Rub hands together until dry.
- Supervise children under 6 years of age when using this product to avoid swallowing.

Other information

- Store below 111 Degree F (43 Degree C)
- May discolor certain fabrics or surfaces

Manufacture By:

Hanoi Biology Chemistry Group Corporation

252/57 Tay Son, Trung Liet Ward, Dong Da District

Hanoi, Vietnam

Inactive ingredients

glycerin, hydrogen peroxide, purified water USP

Package Label - Principal Display Panel

5000 mL NDC: 78185-004-01